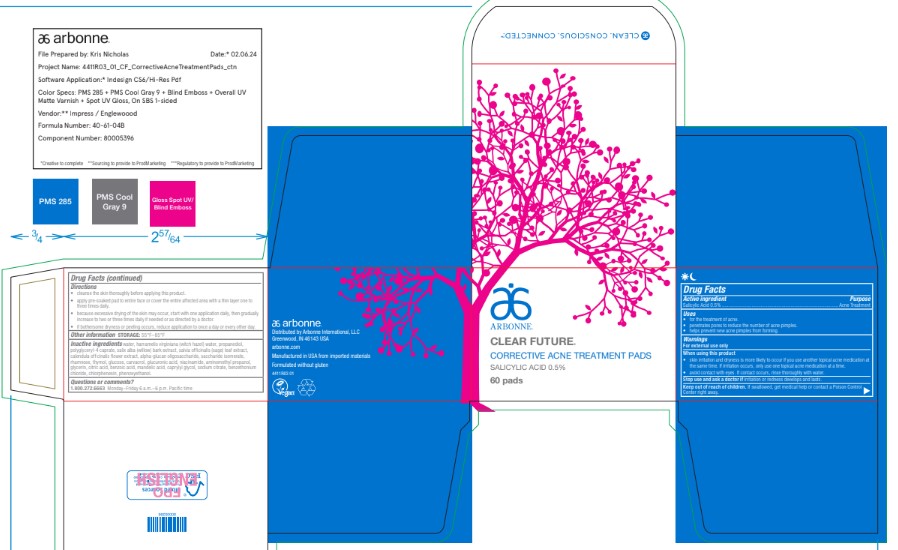 DRUG LABEL: Clear Future Corrective Treatment
NDC: 42508-104 | Form: CLOTH
Manufacturer: Arbonne International, LLC
Category: otc | Type: HUMAN OTC DRUG LABEL
Date: 20251203

ACTIVE INGREDIENTS: SALICYLIC ACID 0.5 mg/90 mL
INACTIVE INGREDIENTS: WATER; HAMAMELIS VIRGINIANA TOP WATER; PROPANEDIOL; POLYGLYCERYL-4 CAPRATE; SALIX ALBA BARK; SAGE; CALENDULA OFFICINALIS FLOWER; .ALPHA.-GLUCAN OLIGOSACCHARIDE; SACCHARIDE ISOMERATE; RHAMNOSE; THYMOL; DEXTROSE, UNSPECIFIED FORM; CARVACROL; GLUCURONIC ACID; NIACINAMIDE; AMINOMETHYLPROPANOL; GLYCERIN; CITRIC ACID MONOHYDRATE; BENZOIC ACID; MANDELIC ACID; CAPRYLYL GLYCOL; SODIUM CITRATE, UNSPECIFIED FORM; BENZETHONIUM CHLORIDE; CHLORPHENESIN; PHENOXYETHANOL

Clear Future®Corrective Treatment

Drug Facts

Active ingredient

Salicylic Acid 0.5%

Purpose

Acne Treatment

Uses

- for the treatment of acne.
- penetrates pores to reduce the number of acne pimples.
- helps prevent new acne pimples from forming.

Warnings

For external use only

When using this product

- skin irritation and dryness is more likely to occur if you use another topical acne medication at the same time. If irritation occurs, only use one topical acne medication at a time.
- avoid contact with eyes. If contact occurs, rinse thoroughly with water.

Stop use and ask a doctor if irritation or redness develops and lasts.

Keep out of reach of children. If swallowed, get medical help or contact a Poison Control Center right away.

Directions

- cleanse the skin thoroughly before applying this product.
- apply pre-soaked pad to entire face or cover the entire affected area with a thin layer one to three times daily.
- because excessive drying of the skin may occur, start with one application daily, then gradually increase to two or three times daily if needed or as directed by a doctor.
- if bothersome dryness or peeling occurs, reduce application to once a day or every other day.

Other information

STORAGE: 55°F–85°F

Inactive ingredients

water, hamamelis virginiana (witch hazel) water, propanediol, polyglyceryl-4 caprate, salix alba (willow) bark extract, salvia officinalis (sage) leaf extract, calendula officinalis flower extract, alpha-glucan oligosaccharide, saccharide isomerate, rhamnose, thymol, glucose, carvacrol, glucuronic acid, niacinamide, aminomethyl propanol, glycerin, citric acid, benzoic acid, mandelic acid, caprylyl glycol, sodium citrate, benzethonium chloride, chlorphenesin, phenoxyethanol.

Questions or comments?

1.800.272.6663 Monday–Friday 6 a.m.–6 p.m. Pacific time

Distributed by Arbonne International, LLC
Greenwood, IN 46143 USA

PRINCIPAL DISPLAY PANEL - 60 Pad Jar Carton

ARBONNE®

CLEAR FUTURE®

CORRECTIVE ACNE TREATMENT PADS

SALICYLIC ACID 0.5%

60 pads